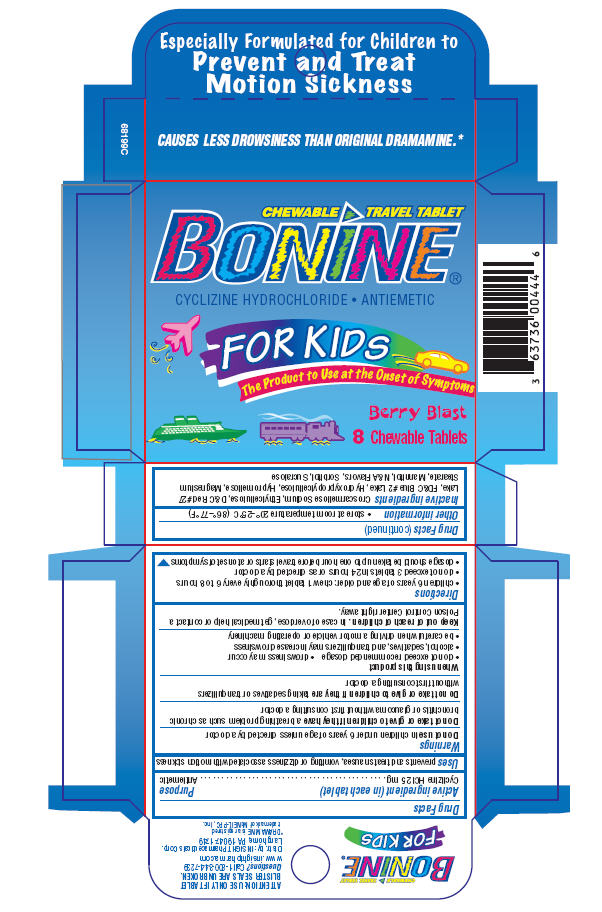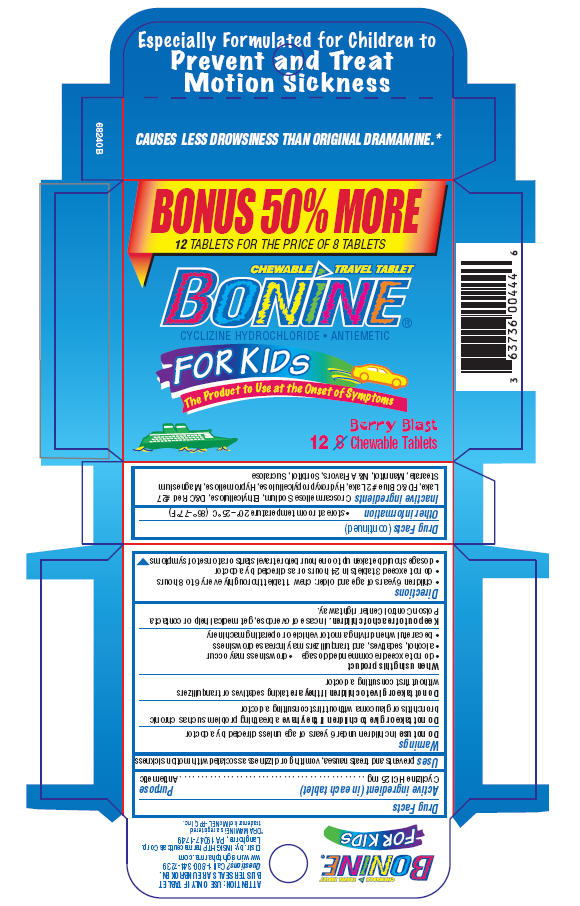 DRUG LABEL: Bonine
NDC: 63736-044 | Form: TABLET, CHEWABLE
Manufacturer: Insight Pharmaceuticals
Category: otc | Type: HUMAN OTC DRUG LABEL
Date: 20090617

ACTIVE INGREDIENTS: Chlorcyclizine Hydrochloride 25 mg/1 1
INACTIVE INGREDIENTS: Crospovidone; FD&C Red No. 40; Aluminum Oxide; Lactose; Magnesium Stearate; Silicon Dioxide; Saccharin Sodium; Stearic Acid; vanilla

CHEWABLE TRAVEL TABLET
BONINE®
FOR KIDS

ATTENTION: USE ONLY IF TABLET BLISTER SEALS ARE UNBROKEN.

Questions? Call 1-800-344-7239
www.insightpharma.com

Distr. by: INSIGHT Pharmaceuticals Corp.
Langhorne, PA 19047-1749

*DRAMAMINE is a registered trademark of McNEIL-PPC, Inc.

Drug Facts

Active ingredient (in each tablet)

Purpose

Cyclizine HCl 25 mg . . . . . . . . . . . . . . . . . . . . . . . . . . . . . . . . . . . . . . . . . . . . Antiemetic

Uses

prevents and treats nausea, vomiting or dizziness associated with motion sickness

Warnings

Do not use in children under 6 years of age unless directed by a doctor

ASK DOCTOR

Do not take or give to children if they have a breathing problem such as chronic bronchitis or glaucoma without first consulting a doctor

Do not take or give to children if they are taking sedatives or tranquilizers without first consulting a doctor

When using this product

- do not exceed recommended dosage
- drowsiness may occur
- alcohol, sedatives, and tranquilizers may increase drowsiness
- be careful when driving a motor vehicle or operating machinery

Keep out of reach of children. In case of overdose, get medical help or contact a Poison Control Center right away.

Directions

- children 6 years of age and older: chew 1 tablet thoroughly every 6 to 8 hours
- do not exceed 3 tablets in 24 hours or as directed by a doctor
- dosage should be taken up to one hour before travel starts or at onset of symptoms

Other information

- store at room temperature 20°–25°C (86°–77°F)

Inactive ingredients

Croscarmellose Sodium, Ethylcellulose, D&C Red #27 Lake, FD&C Blue #2 Lake, Hydroxypropylcellulose, Hypromellose, Magnesium Stearate, Mannitol, N&A Flavors, Sorbitol, Sucralose

PRINCIPAL DISPLAY PANEL - Box of 8 Tablets

CHEWABLE TRAVEL TABLET
BONINE®

CYCLIZINE HYDROCHLORIDE • ANTIEMETIC

FOR KIDS
The Product to Use at the Onset of Symptoms

Berry Blast

8 Chewable Tablets

PRINCIPAL DISPLAY PANEL - Box of 12 Tablets

BONUS 50% MORE
12 TABLETS FOR THE PRICE OF 8 TABLETS

CHEWABLE TRAVEL TABLET
BONINE®

CYCLIZINE HYDROCHLORIDE • ANTIEMETIC

FOR KIDS
The Product to Use at the Onset of Symptoms

Berry Blast

12 Chewable Tablets